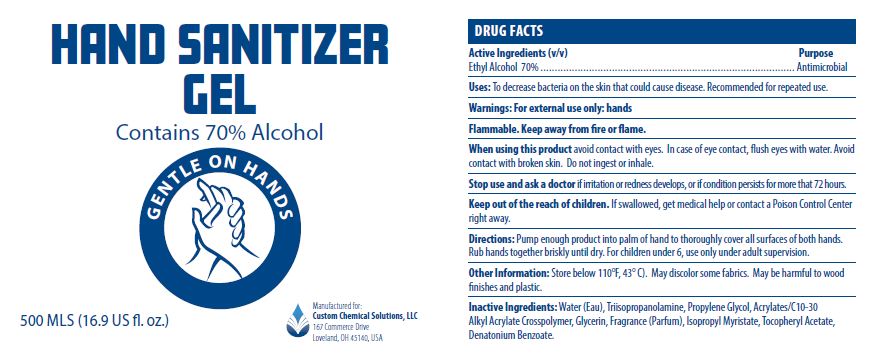 DRUG LABEL: HAND SANITIZER
NDC: 77955-003 | Form: GEL
Manufacturer: Custom Chemicial Solutions
Category: otc | Type: HUMAN OTC DRUG LABEL
Date: 20240122

ACTIVE INGREDIENTS: ALCOHOL 70 mL/100 mL
INACTIVE INGREDIENTS: GLYCERIN; CARBOMER INTERPOLYMER TYPE A (55000 CPS); .ALPHA.-TOCOPHEROL ACETATE; WATER; ISOPROPYL MYRISTATE; TRIISOPROPANOLAMINE; PROPYLENE GLYCOL; DENATONIUM BENZOATE

77955-003

Active ingredients (v/v)

Ethyl Alcohol 70%

Purpose

Antimicrobial

Uses:

To decrease bacteria on the skin that could cause disease.

Recommended for repeated use.

Warnings

For external use only: hands

Flammable. Keep away from fire or flame.

When using this productavoid contact with eyes.

In case of eye contact, flush eyes with water.

Avoid contact with broken skin.

Do not ingest or inhale.

Stop use and ask a doctorif irritation or redness develops, or if condition persists for more than 72 hours.

Keep out of reach of children.

If swallowed, get medical help or contact a Poison Control Center right away.

Directions:

Pump enough product into palm of hand to thoroughly cover all surfaces of both hands.

Rub hands together briskly until dry.

For children under 6, use only under adult supervision

Other Information:

Store below 110 F (43 C).

May discolor some fabrics.

May be harmful to wood finishes and plastics.

Inactive ingredients:

Water (Eau), Triisopropanolamine, Propylene Glycol, Acrylates/C10-30 Alkyl Acrylate Crosspolymer, Glycerin, Fragrance (Parfum), Isopropyl Myristate, Tocopheryl Acetate, Denatonium Benzoate.

PACKAGE LABEL

HAND SANITIZER

GEL

Contains 70% Alcohol

GENTLE ON HANDS

500 MLS (16.9 US fl. oz)

Manfactured for:

Custom Chemical Solutions, LLC

167 Commerce Drive

Loveland, OH 45140